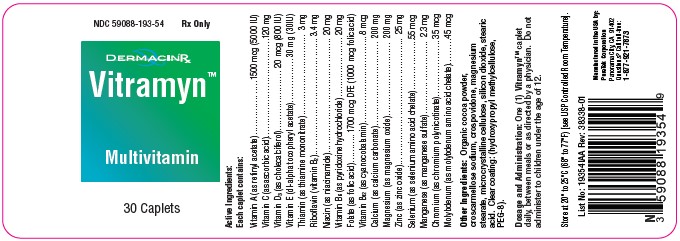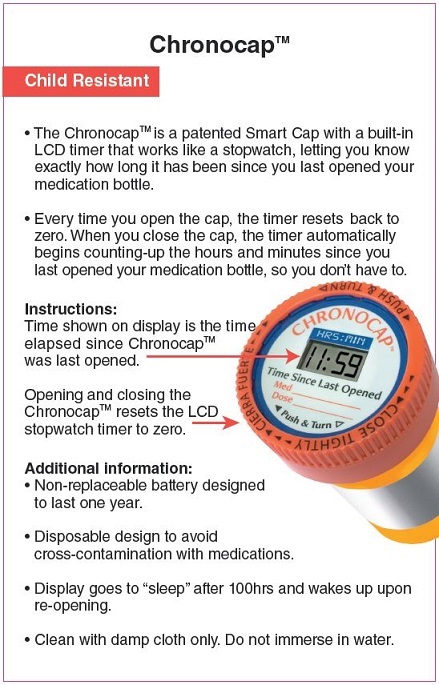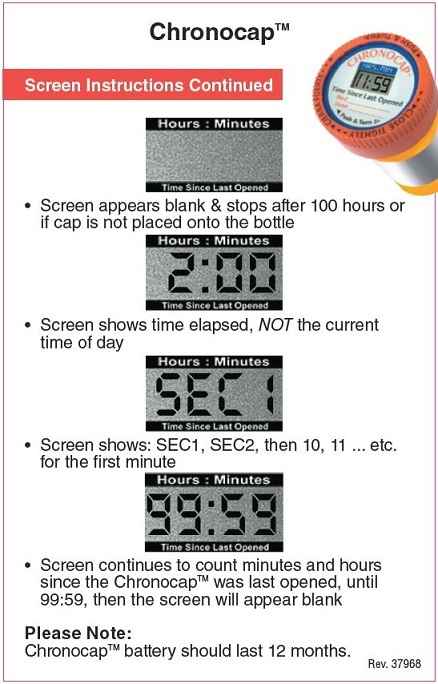 DRUG LABEL: Vitramyn
NDC: 59088-193 | Form: TABLET
Manufacturer: PureTek Corporation
Category: prescription | Type: HUMAN PRESCRIPTION DRUG LABEL
Date: 20241203

ACTIVE INGREDIENTS: RIBOFLAVIN 3.4 mg/1 1; NIACINAMIDE 20 mg/1 1; ASCORBIC ACID 120 mg/1 1; FOLIC ACID 1000 ug/1 1; CYANOCOBALAMIN 8 ug/1 1; CALCIUM CARBONATE 200 mg/1 1; VITAMIN A ACETATE 1500 ug/1 1; THIAMINE MONONITRATE 3 mg/1 1; ZINC OXIDE 25 mg/1 1; MANGANESE SULFATE 2.3 mg/1 1; .ALPHA.-TOCOPHEROL ACETATE, DL- 30 mg/1 1; MAGNESIUM OXIDE 200 mg/1 1; CHROMIUM NICOTINATE 35 ug/1 1; PYRIDOXINE HYDROCHLORIDE 20 mg/1 1; MOLYBDENUM 45 ug/1 1; SELENIUM 55 ug/1 1; CHOLECALCIFEROL 20 ug/1 1
INACTIVE INGREDIENTS: MAGNESIUM STEARATE; HYPROMELLOSES; POLYETHYLENE GLYCOL 400; COCOA; CROSPOVIDONE; STEARIC ACID; MICROCRYSTALLINE CELLULOSE; SILICON DIOXIDE; CROSCARMELLOSE SODIUM

Vitramyn Rx
Multivitamin
Rx Only

DESCRIPTION:

Each caplet contains:

Vitamin A (as retinyl acetate)……………….. 1500 mcg (5000 IU)
Vitamin C (as ascorbic acid)……………….……………… 120 mg
Vitamin D3 (as cholecalciferol)…………….……. 20 mcg (800 IU)
Vitamin E (dl-alpha tocopheryl acetate)……………. 30 mg (30IU)
Thiamin (as thiamine mononitrate)…………...……………… 3 mg
Riboflavin (vitamin B2)…………………………...…………. 3.4 mg
Niacin (as niacinamide)…………………………....………… 20 mg
Vitamin B6 (as pyridoxine hydrochloride)………….………. 20 mg
Folate (as folic acid)……….. 1700 mcg DFE (1000 mcg folic acid)
Vitamin B12 (as cyanocobalamin)………………….……….. 8 mcg
Calcium (as calcium carbonate)……………………...……. 200 mg
Magnesium (as magnesium oxide)……………………...… 200 mg
Zinc (as zinc oxide)………………………………………....... 25 mg
Selenium (as selenium amino acid chelate)……………….55 mcg
Manganese (as manganese sulfate)………………………. 2.3 mg
Chromium (as chromium polynicotinate)………………..... 35 mcg
Molybdenum (as molybdenum amino acid chelate)……... 45 mcg

Other Ingredients:
Organic cocoa powder, croscarmellose sodium, crospovidone, magnesium stearate, microcrystalline cellulose, silicon dioxide, stearic acid. Clear coating: (hydroxypropyl methylcellulose, PEG-8).

Indications and Usage:

Vitramyn™ is indicated to provide vitamin supplements to men and women. Folic acid is effective in the treatment of megaloblastic anemias due to a deficiency of folic acid (as may be seen in tropical or nontropical sprue) and in anemias of nutritional origin, pregnancy, infancy, or childhood.

Contraindications:

This product is contraindicated in patients with a known hypersensitivity to any of the ingredients.

WARNING:

Administration of folic acid alone is improper therapy for pernicious anemia and other megaloblastic anemias in which vitamin B12 is deficient.

Precautions:

Folic acid in doses above 0.1 mg daily may obscure pernicious anemia, in that hematologic remission can occur while neurological manifestations remain progressive.
There is a potential danger in administering folic acid to patients with undiagnosed anemia, since folic acid may obscure the diagnosis of pernicious anemia by alleviating the hematologic manifestations of the disease while allowing the neurologic complications to progress. This may result in severe nervous system damage before the correct diagnosis is made. Adequate doses of vitamin B12 may prevent, halt, or improve the neurologic changes caused by pernicious anemia.
The patient’s medical conditions and consumption of other drugs, herbs, and/or supplements should be considered.

For use on the order of a healthcare practitioner.
Call your doctor about side effects. To report side effects, call PureTek Corporation at 1-877-921-7873 or FDA at 1-800-FDA-1088 or
www.fda.gov/medwatch

Drug Interactions:

Vitramyn™ is not recommended for and should not be given to patients receiving levodopa because the action of levodopa is antagonized by pyridoxine. There is a possibility of increased bleeding due to pyridoxine interaction with anticoagulants (e.g., Aspirin, Heparin, or Clopidogrel).

Adverse Reactions:

Allergic sensitization has been reported following both oral and parenteral administration of folic acid.

Adverse reactions have been reported with specific vitamins and minerals but generally at levels substantially higher than those contained herein. However, allergic and idiosyncratic reactions are possible at lower levels. Iron, even at the usual recommended levels, has been associated with gastrointestinal intolerance in some patients.

Dosage and Administration:

One (1) Vitramyn™ caplet daily, between meals or as directed by a physician. Do not administer to children under the age of 12.

How Supplied:

Vitramyn™ are beige speckled, oblong, coated caplets in bottles containing 30 caplets – NDC 59088-193-54. Dispense in a tight, light-resistant container as defined in the USP/NF with a child-resistant closure. Store at controlled room temperature 20° to 25°C (68° to 77°F). [See USP]. Protect from light and moisture and avoid excessive heat.

Storage

Do not use if bottle seal is broken.
KEEP THIS AND ALL MEDICATIONS OUT OF THE REACH OF CHILDREN.
Store at controlled room temperature 20° to 25°C (68° to 77°F). [See USP].
Protect from light and moisture and avoid excessive heat.
To report a serious adverse event or to obtain product information, contact
877-921-7873.

Vitramyn™

Manufactured in the USA by:
PureTek Corporation
Panorama City, CA 91402
Questions? Call toll-free:
1-877-921-7873